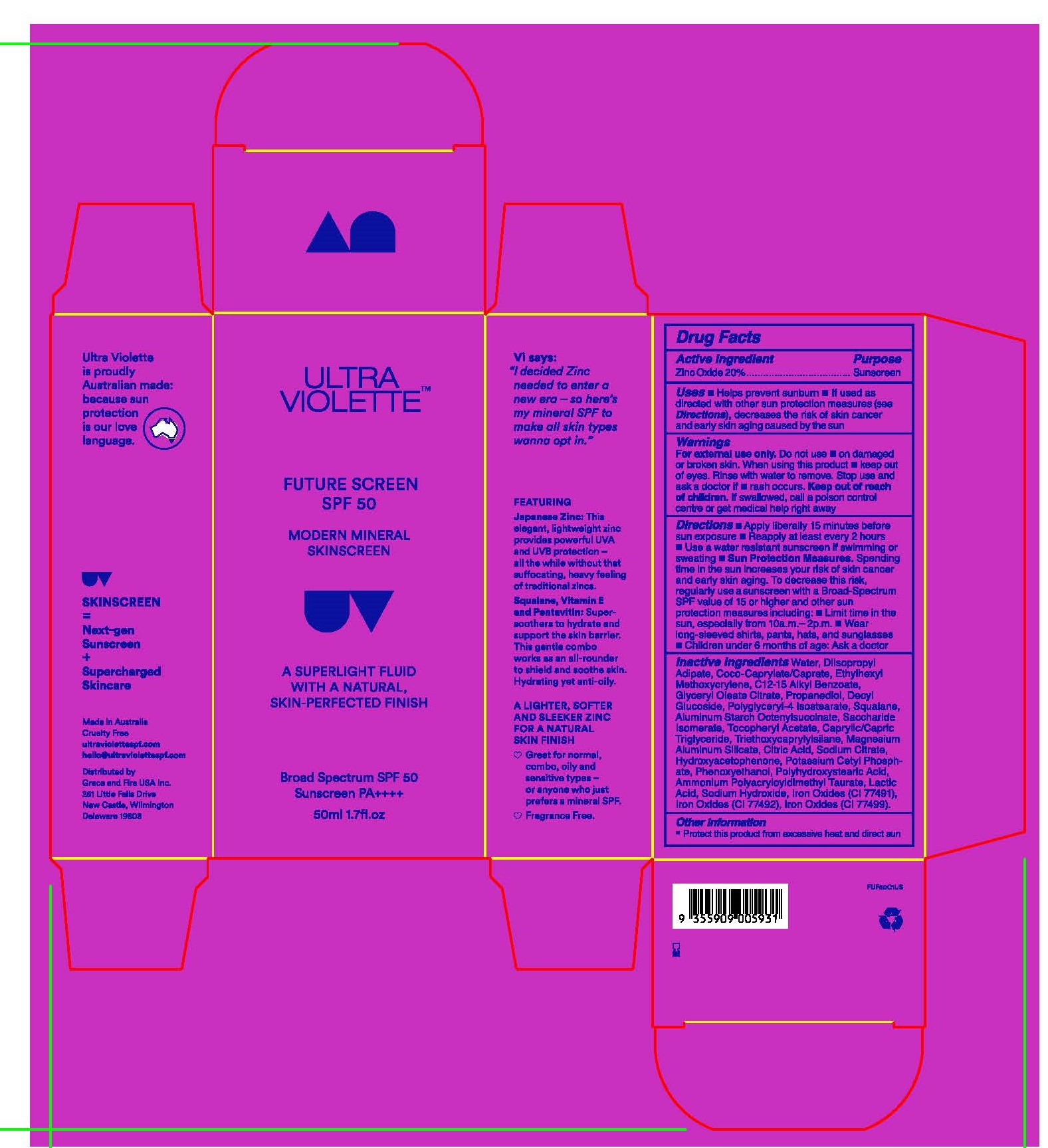 DRUG LABEL: Ultra Violette Future Screen Broad Spectrum SPF 50
NDC: 84803-103 | Form: LOTION
Manufacturer: Grace and Fire USA Inc.
Category: otc | Type: HUMAN OTC DRUG LABEL
Date: 20260119

ACTIVE INGREDIENTS: ZINC OXIDE 200 mg/1 mL
INACTIVE INGREDIENTS: C12-15 ALKYL BENZOATE; COCO-CAPRYLATE/CAPRATE; CI 77499; SODIUM CITRATE; SQUALANE; CI 77492; LACTIC ACID; ETHYLHEXYL METHOXYCRYLENE; MAGNESIUM ALUMINUM SILICATE; SODIUM HYDROXIDE; TRIETHOXYCAPRYLYLSILANE; HYDROXYACETOPHENONE; WATER; GLYCERYL OLEATE CITRATE; SACCHARIDE ISOMERATE; POLYHYDROXYSTEARIC ACID (2300 MW); DIISOPROPYL ADIPATE; ALPHA-TOCOPHEROL ACETATE; POLYGLYCERYL-4 ISOSTEARATE; PROPANEDIOL; CAPRYLIC/CAPRIC TRIGLYCERIDE; CITRIC ACID; DECYL GLUCOSIDE; POTASSIUM CETYL PHOSPHATE; ALUMINUM STARCH OCTENYLSUCCINATE; PHENOXYETHANOL; AMMONIUM POLYACRYLOYLDIMETHYL TAURATE; CI 77491

ACTIVE INGREDIENTS

ZINC OXIDE 20%

PURPOSE

SUNSCREEN

USE

HELPS PREVENT SUNBURN

If used as directed with other sun protection measures (see Directions), decreases the risk of skin cancer and early skin aging caused by the sun

WARNINGS

DO NOT USE

on damaged or broken skin

WHEN USING THIS PRODUCT

keep out of eyes. Rinse with water to remove.

STOP USE AND ASK A DOCTOR IF

rash occurs

KEEP OUT OF REACH OF CHILDREN

If swallowed, get medical help or contact a Poison Control Center right away

Directions

- apply liberally and evenly 15 minutes before sun exposure
- reapply at least every 2 hours
- use a water resistant sunscreen if swimming or sweating
- Sun Protection Measures. Spending time in the sun increases your risk of skin cancer and early skin aging. To decrease this risk, regularly use a sunscreen with a Broad Spectrum SPF value of 15 or higher and other sun protection measures including:
- limit time in the sun, especially from 10 a.m. – 2 p.m.
- wear long-sleeved shirts, pants, hats, and sunglasses
- children under 6 months of age: Ask a doctor

Inactive Ingredients

Water, Diisopropyl Adipate, Coco-Caprylate/Caprate, Ethylhexyl Methoxycrylene, C12-15 Alkyl Benzoate, Glyceryl Oleate Citrate, Propanediol, Decyl Glucoside, Polyglyceryl-4 Isostearate, Squalane, Aluminum Starch Octenylsuccinate, Saccharide Isomerate, Tocopheryl Acetate, Caprylic/Capric Triglyceride, Triethoxycaprylylsilane, Magnesium Aluminum Silicate, Citric Acid, Sodium Citrate, Hydroxyacetophenone, Potassium Cetyl Phosphate, Phenoxyethanol, Polyhydroxystearic Acid, Ammonium Polyacryloyldimethyl Taurate, Lactic Acid, Sodium Hydroxide, Iron Oxides (CI 77491), Iron Oxides (CI 77492), Iron Oxides (CI 77499)

Other Information

Protect this product from excessive heat and direct sun

Principal Display Panel

Ultra Violette

Future Screen Broad Spectrum SPF 50

1.7 FL. OZ. (50 mL)